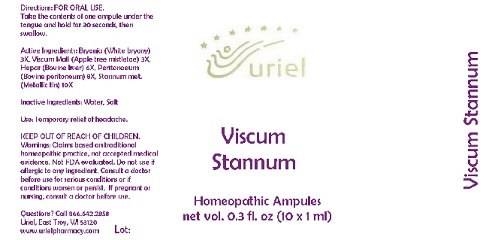 DRUG LABEL: Viscum Stannum
NDC: 48951-9144 | Form: LIQUID
Manufacturer: Uriel Pharmacy Inc.
Category: homeopathic | Type: HUMAN OTC DRUG LABEL
Date: 20180514

ACTIVE INGREDIENTS: BRYONIA ALBA ROOT 3 [hp_X]/1 mL; VISCUM ALBUM FRUITING TOP 3 [hp_X]/1 mL; MAMMAL LIVER 6 [hp_X]/1 mL; BEEF 8 [hp_X]/1 mL; TIN 10 [hp_X]/1 mL
INACTIVE INGREDIENTS: WATER; SODIUM CHLORIDE

Viscum Stannum

INDICATIONS AND USAGE

Directions: FOR ORAL USE.

DOSAGE AND ADMINISTRATION

Take the contents of one ampule under the tongue and hold for 30 seconds, then swallow.

ACTIVE INGREDIENT

Active Ingredients: Bryonia (White bryony) 3X, Viscum Mali (Apple tree mistletoe) 3X, Hepar (Bovine liver) 6X, Peritonaeum (Bovine peritoneum) 8X, Stannum met. (Metallic tin) 10X

Inactive Ingredients: Water, Salt

PURPOSE

Use: Temporary relief of headache.

KEEP OUT OF REACH OF CHILDREN.

WARNINGS

Warnings: Claims based on traditional homeopathic practice, not accepted medical evidence. Not FDA evaluated. Do not use if allergic to any ingredient. Consult a doctor before use for serious conditions or if conditions worsen or persist. If pregnant or nursing, consult a doctor before use.

QUESTIONS

Questions? Call 866.642.2858 Uriel, East Troy, WI 53120 www.urielpharmacy.com